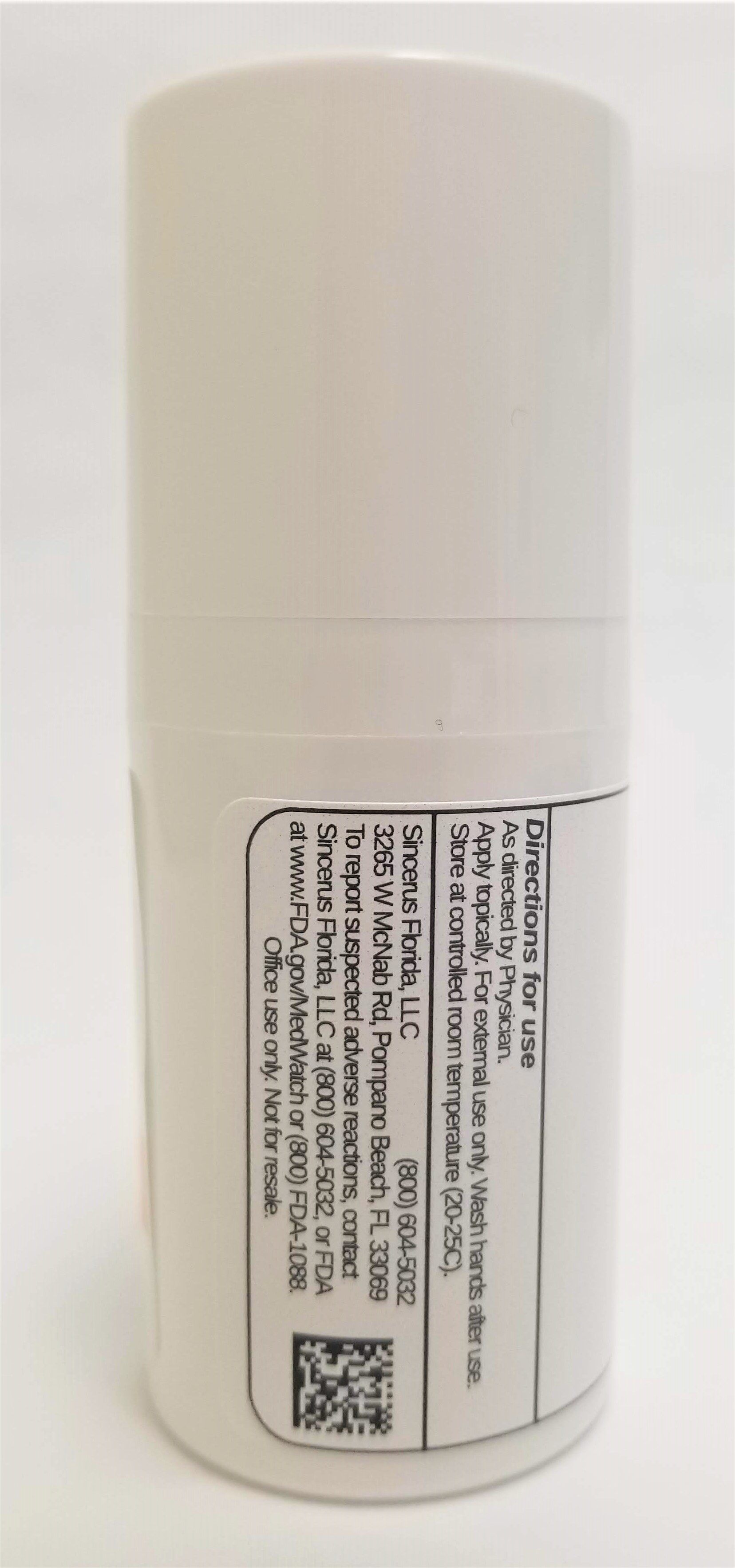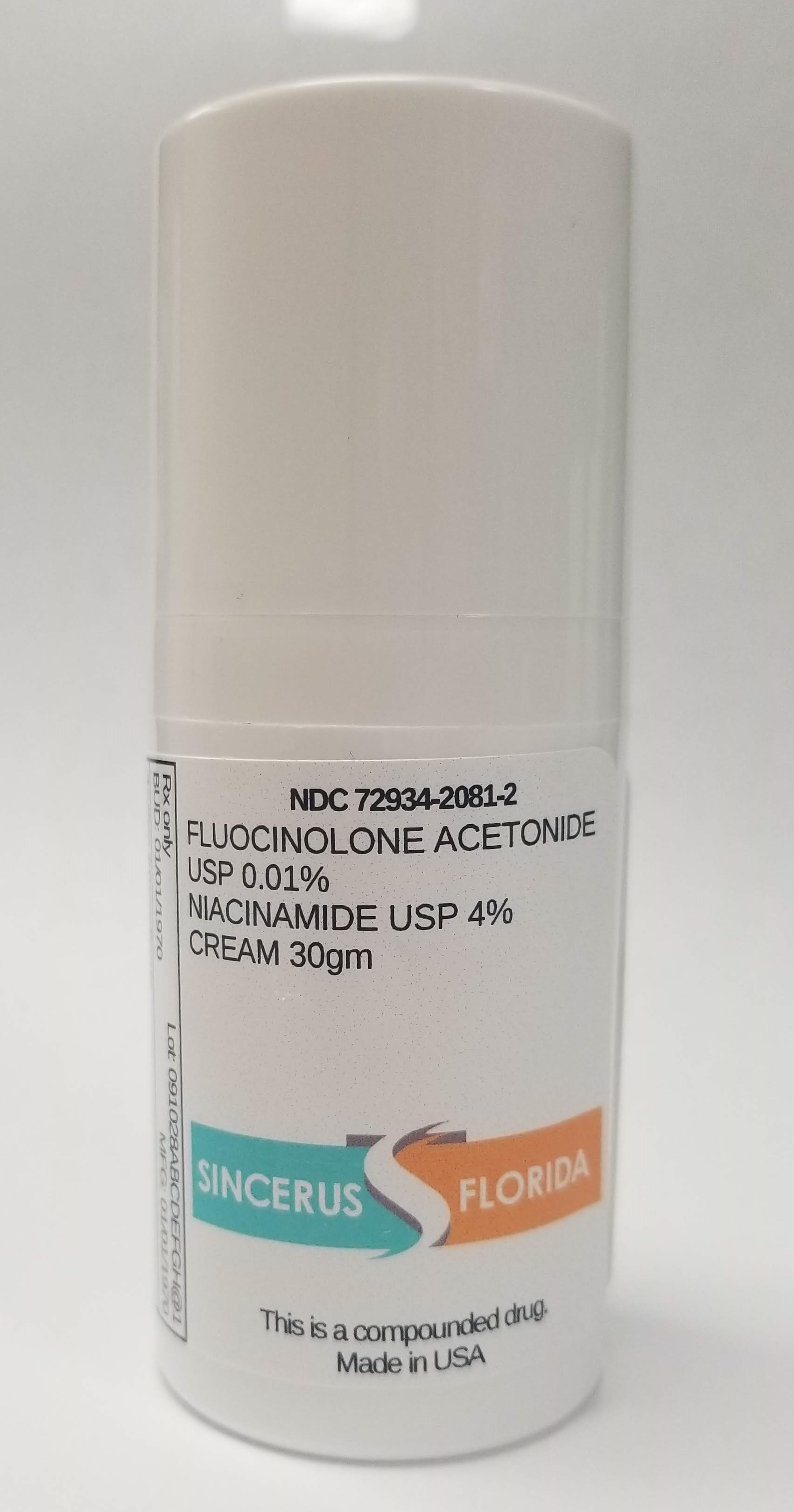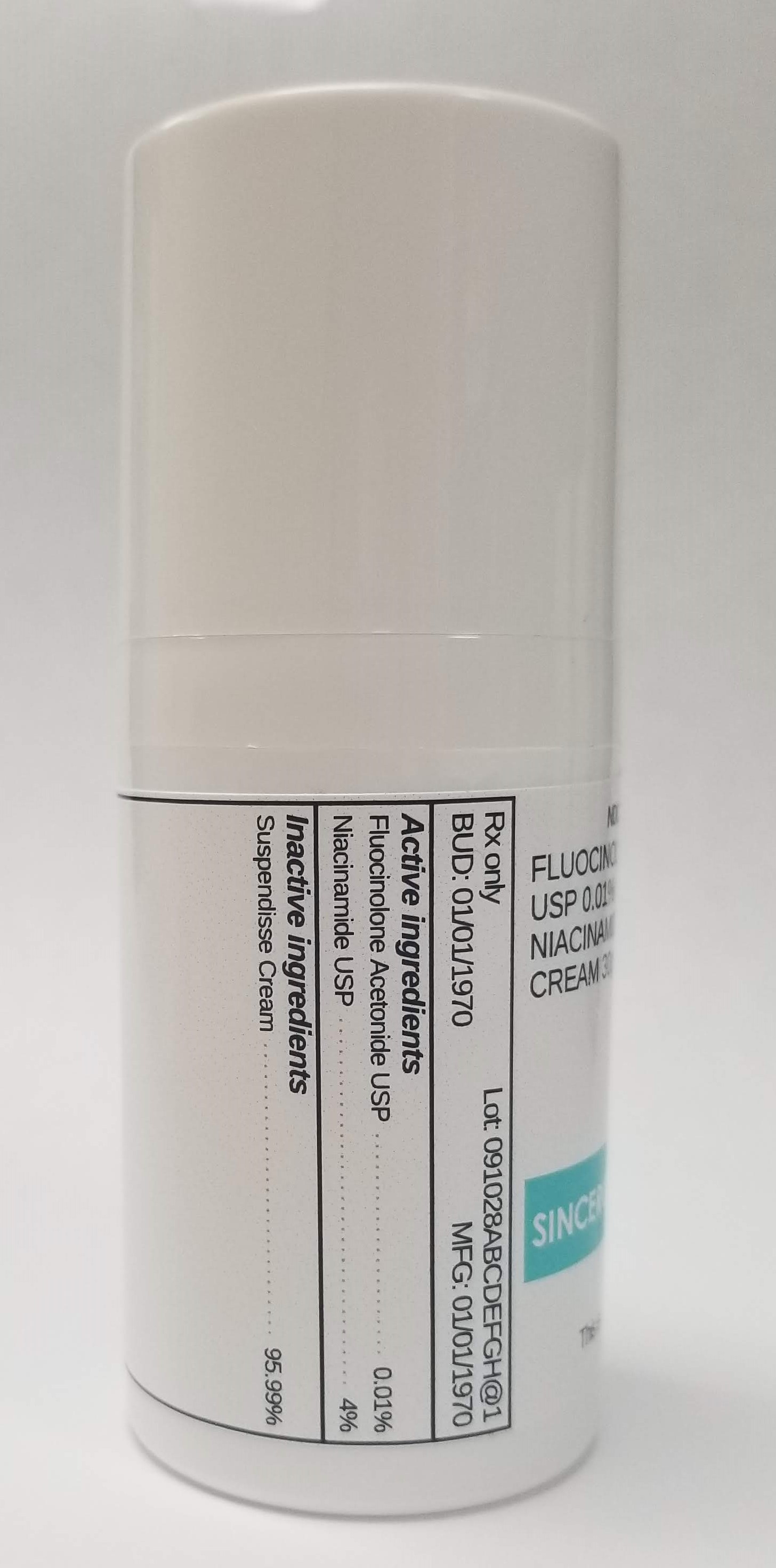 DRUG LABEL: FLUOCINOLONE ACETONIDE 0.01% / NIACINAMIDE 4%
NDC: 72934-2081 | Form: CREAM
Manufacturer: Sincerus Florida LLC
Category: prescription | Type: HUMAN PRESCRIPTION DRUG LABEL
Date: 20190513

ACTIVE INGREDIENTS: FLUOCINOLONE ACETONIDE 0.01 g/100 g; NIACINAMIDE 4 g/100 g

FLUOCINOLONE ACETONIDE 0.01% / NIACINAMIDE 4%